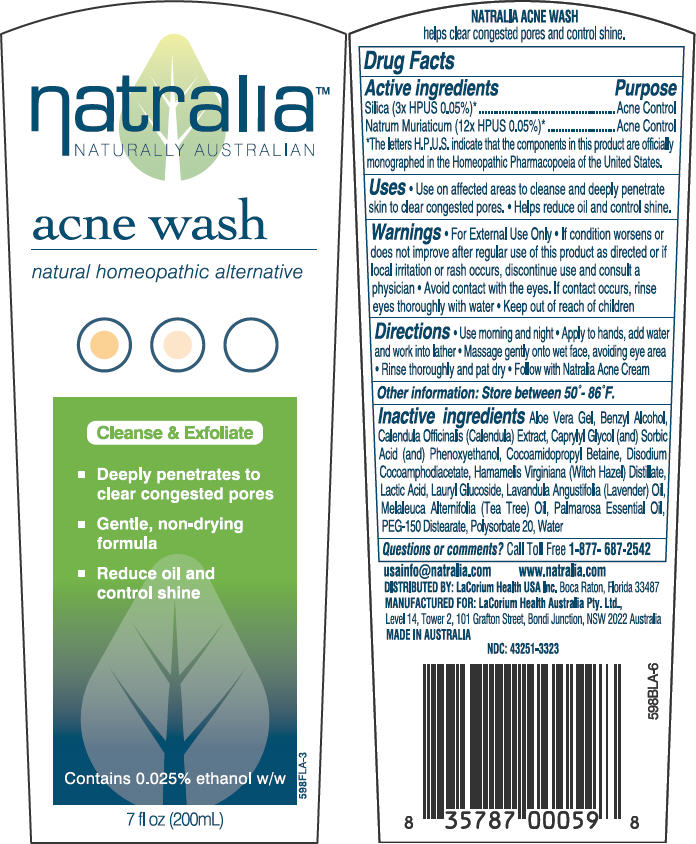 DRUG LABEL: natralia
NDC: 43251-3323 | Form: LIQUID
Manufacturer: LaCorium Health International Pty Ltd
Category: homeopathic | Type: HUMAN OTC DRUG LABEL
Date: 20121219

ACTIVE INGREDIENTS: SILICON DIOXIDE 3 [hp_X]/1 mL; SODIUM CHLORIDE 12 [hp_X]/1 mL
INACTIVE INGREDIENTS: ALOE VERA LEAF; BENZYL ALCOHOL; CALENDULA OFFICINALIS FLOWER; COCAMIDOPROPYL BETAINE; LACTIC ACID; LAURYL GLUCOSIDE; LAVANDULA ANGUSTIFOLIA FLOWERING TOP; CAPRYLYL GLYCOL; SORBIC ACID; PHENOXYETHANOL; PALMAROSA OIL; PEG-150 DISTEARATE; POLYSORBATE 20; TEA TREE OIL; WITCH HAZEL; DISODIUM COCOAMPHODIACETATE

natralia™
NATURALLY AUSTRALIAN

acne wash

Drug Facts

ACTIVE INGREDIENT

Active ingredients | Purpose
Silica (3× HPUS 0.05%) [The letters H.P.U.S. indicate that the components in this product are officially monographed in the Homeopathic Pharmacopoeia of the United States.] | Acne Control
Natrum Muriaticum (12× HPUS 0.05%) | Acne Control

Uses

- Use on affected areas to cleanse and deeply penetrate skin to clear congested pores.
- Helps reduce oil and control shine.

Warnings

- For External Use Only

STOP USE

- If condition worsens or does not improve after regular use of this product as directed or if local irritation or rash occurs, discontinue use and consult a physician

WHEN USING

- Avoid contact with the eyes. If contact occurs, rinse eyes thoroughly with water

- Keep out of reach of children

Directions

- Use morning and night
- Apply to hands, add water and work into lather
- Massage gently onto wet face, avoiding eye area
- Rinse thoroughly and pat dry
- Follow with Natralia Acne Cream

Other information

Store between 50°- 86°F.

Inactive ingredients

Aloe Vera Gel, Benzyl Alcohol, Calendula Officinalis (Calendula) Extract, Caprylyl Glycol (and) Sorbic Acid (and) Phenoxyethanol, Cocoamidopropyl Betaine, Disodium Cocoamphodiacetate, Hamamelis Virginiana (Witch Hazel) Distillate, Lactic Acid, Lauryl Glucoside, Lavandula Angustifolia (Lavender) Oil, Melaleuca Alternifolia (Tea Tree) Oil, Palmarosa Essential Oil, PEG-150 Distearate, Polysorbate 20, Water

Questions or comments?

Call Toll Free 1-877- 687-2542

PRINCIPAL DISPLAY PANEL - 200mL Tube Label

natralia™
NATURALLY AUSTRALIAN

acne wash

natural homeopathic alternative

Cleanse & Exfoliate

- Deeply penetrates to
  clear congested pores
- Gentle, non-drying
  formula
- Reduce oil and
  control shine

Contains 0.025% ethanol w/w

7 fl oz (200mL)

598FLA-3